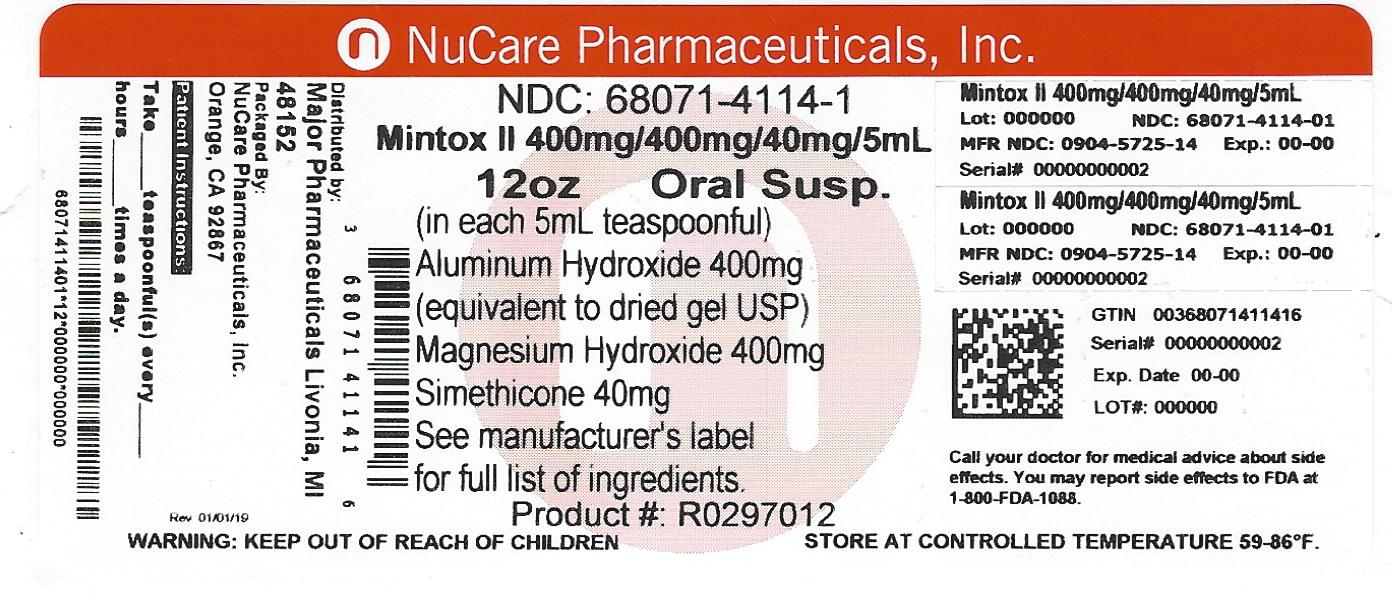 DRUG LABEL: MINTOX MAXIMUM STRENGTH
NDC: 68071-4114 | Form: SUSPENSION
Manufacturer: NuCare Pharmaceuticals,Inc.
Category: otc | Type: HUMAN OTC DRUG LABEL
Date: 20240604

ACTIVE INGREDIENTS: ALUMINUM HYDROXIDE 400 mg/5 mL; MAGNESIUM HYDROXIDE 400 mg/5 mL; DIMETHICONE 40 mg/5 mL
INACTIVE INGREDIENTS: BENZYL ALCOHOL; BUTYLPARABEN; CARBOXYMETHYLCELLULOSE SODIUM; HYPROMELLOSES; CELLULOSE, MICROCRYSTALLINE; PROPYLPARABEN; WATER; SORBITOL; D&C YELLOW NO. 10; GLYCERIN

Active ingredients (in each 5 mL teaspoonful)

Aluminum hydroxide 400 mg (equivalent to dried gel, USP)

Magnesium hydroxide 400 mg

Simethicone 40mg

Purposes

Antacid

Antigas

Uses

relieves

- heartburn
- sour stomach
- acid indigestion
- the symptoms referred to as gas

Warnings

Ask a doctor before use if you have

• kidney disease

• a magnesium-restricted diet

Ask a doctor or pharmacist before use if you are taking a prescription drug.

Antacids may interact with certain prescription drugs.

Stop use and ask a doctor if symptoms last more than 2 weeks

If pregnant or breast-feeding, ask a health professional before use.

Keep out of reach of children.

Directions

• shake well before use

• do not take more than 8 teaspoonfuls in 24 hours or use the maximum dosage for more than 2 weeks

• adults and children 12 years and older: take 2 to 4 teaspoonfuls two times a day, or as directed by a doctor

• children under 12 years: ask a doctor

Other information

• each 5 mL teaspoonful contains: magnesium 165 mg, sodium 1 mg

• store at room temperature

• protect from freezing

• keep tightly closed

• TAMPER-EVIDENT: Do not use if breakaway band on bottle cap is missing or broken.

Inactive ingredients

benzyl alcohol, butylparaben, caramel color, carboxymethylcellulose sodium, D and C yellow no.10, flavor, glycerin, hypromellose, microcrystalline cellulose, propylparaben, purified water, saccharin sodium, sorbitol solution